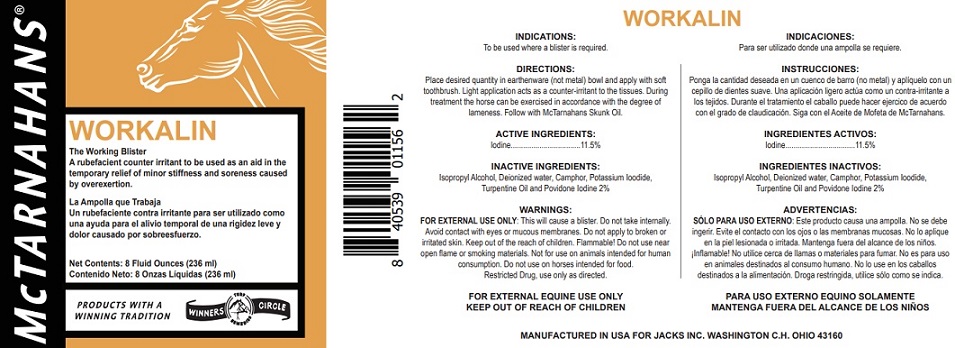 DRUG LABEL: WORKALIN
NDC: 61156-211 | Form: LINIMENT
Manufacturer: JACKS MFG INC
Category: animal | Type: OTC ANIMAL DRUG LABEL
Date: 20211208

ACTIVE INGREDIENTS: IODINE 0.115 g/1 mL
INACTIVE INGREDIENTS: POTASSIUM IODIDE 0.065 g/1 mL; POVIDONE 0.02 g/1 mL; ISOPROPYL ALCOHOL 0.214 mL/1 mL; CAMPHOR (NATURAL) 0.076 g/1 mL; TURPENTINE 0.0267 g/1 mL; WATER 0.496 mL/1 mL

WORKALIN

INDICATIONS

To be used where a blister is required.

DIRECTIONS

Place desired quantity in earthenware (not metal) bowl and apply with soft toothbrush.
Light application acts as a counter-irritant to the tissues.
During treatment the horse can be exercised in accordance with the degree of lameness.
Follow with McTarnahans Skunk Oil.

WARNING

FOR EXTERNAL USE ONLY: This will cause a blister.
Do not take internally.
Avoid contact with eyes or mucous membranes.
Do not apply to broken or irritated skin.
Keep out of the reach of children.
Flammable! Do not use near open flame or smoking materials.
Not for use on animals intended for human consumption.
Do not use on horses intended for food.
Restricted Drug, use only as directed.

FOR EXTERNAL EQUINE USE ONLY
KEEP OUT OF REACH OF CHILDREN